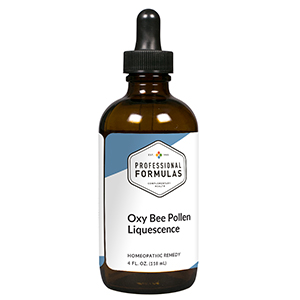 DRUG LABEL: Oxy Bee Pollen Liquescence
NDC: 63083-3012 | Form: LIQUID
Manufacturer: Professional Complementary Health Formulas
Category: homeopathic | Type: HUMAN OTC DRUG LABEL
Date: 20190815

ACTIVE INGREDIENTS: BEE POLLEN 2 [hp_X]/118 mL; ENGLISH SOLE 2 [hp_X]/118 mL; DNA-DIRECTED RNA POLYMERASE SUBUNIT BETA (M. TUBERCULOSIS) 2 [hp_X]/118 mL; BITTER ALMOND 3 [hp_X]/118 mL; FUCUS VESICULOSUS 3 [hp_X]/118 mL; LAMINARIA JAPONICA 3 [hp_X]/118 mL; MEDICAGO SATIVA WHOLE 3 [hp_X]/118 mL; ROYAL JELLY 3 [hp_X]/118 mL; ZINC 4 [hp_X]/118 mL; PANTOTHENIC ACID 6 [hp_X]/118 mL; COMFREY ROOT 6 [hp_X]/118 mL
INACTIVE INGREDIENTS: ALCOHOL; WATER

T12

ACTIVE INGREDIENTS

Bee pollen 2X
Flower pollen 2X
RNA-DNA (yeast) 2X
Amygdala amara 3X
Fucus vesiculosus 3X
Laminaria thallus 3X
Medicago sativa 3X
Royal jelly 3X
Zincum metallicum 4X, 6X
B vitamins (B1, B2, B3, B5, B6, B12) 6X
Symphytum officinale 6X

QUESTIONS

Professional Formulas

PO Box 2034 Lake Oswego, OR 97035

INDICATIONS

For the temporary relief of inflammation, mild pain or stiffness in joints, muscles, or surrounding tissues, irritability, poor concentration, diminished memory, fatigue, or general weakness.*

PURPOSE

*Claims based on traditional homeopathic practice, not accepted medical evidence. Not FDA evaluated.

WARNINGS

In case of overdose, get medical help or contact a poison control center right away.

Keep out of the reach of children.

PREGNANCY OR BREAST FEEDING

If pregnant or breastfeeding, ask a healthcare professional before use.

DIRECTIONS

Place drops under tongue 30 minutes before/after meals. Adults and children 12 years and over: Take one full dropper up to 2 times per day. Consult a physician for use in children under 12 years of age.

OTHER INFORMATION

Tamper resistant. If seal is broken, do not use. After opening, close container tightly and store at room temperature away from heat.

INACTIVE INGREDIENTS

20% ethanol, purified water.

LABEL

Est 1985

Professional Formulas

Complementary Health

Oxy Bee Pollen Liquescence

Homeopathic Remedy

4 FL. OZ. (118 mL)